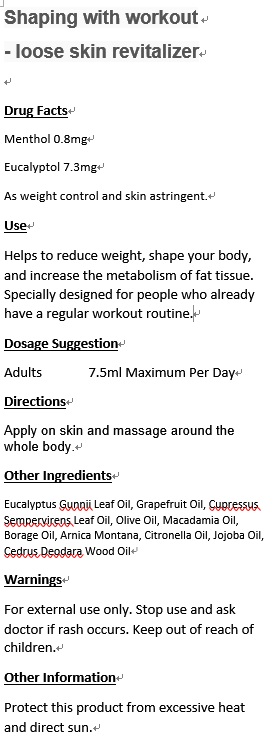 DRUG LABEL: Lactic Acid Free for sportswoman Synergy
NDC: 70470-8005 | Form: OIL
Manufacturer: PHYTOPIA CO., LTD.
Category: otc | Type: HUMAN OTC DRUG LABEL
Date: 20170101

ACTIVE INGREDIENTS: MENTHOL 0.8 mg/50 mL
INACTIVE INGREDIENTS: GRAPEFRUIT OIL; JOJOBA OIL; CHAMOMILE FLOWER OIL; METHYL SALICYLATE; OLIVE OIL; MACADAMIA OIL; CALENDULA OFFICINALIS SEED OIL; ARNICA MONTANA

Drug Facts

Menthol 0.8mg

Eucalyptol 7.3mg

As weight control and skin astringent.

Use

Helps to reduce weight, shape your body, and increase the metabolism of fat tissue. Specially designed for people who already have a regular workout routine.

Dosage Suggestion

Adults 7.5ml Maximum Per Day

Directions

Apply on skin and massage around the whole body.

INACTIVE INGREDIENT

Other Ingredients

Eucalyptus Gunnii Leaf Oil, Grapefruit Oil, Cupressus Sempervirens Leaf Oil, Olive Oil, Macadamia Oil, Borage Oil, Arnica Montana, Citronella Oil, Jojoba Oil, Cedrus Deodara Wood Oil

Warnings

For external use only. Stop use and ask doctor if rash occurs. Keep out of reach of children.

Warnings

For external use only. Stop use and ask doctor if rash occurs. Keep out of reach of children.

Other Information

Protect this product from excessive heat and direct sun.

PACKAGE LABEL

Shaping with workout

- loose skin revitalizer